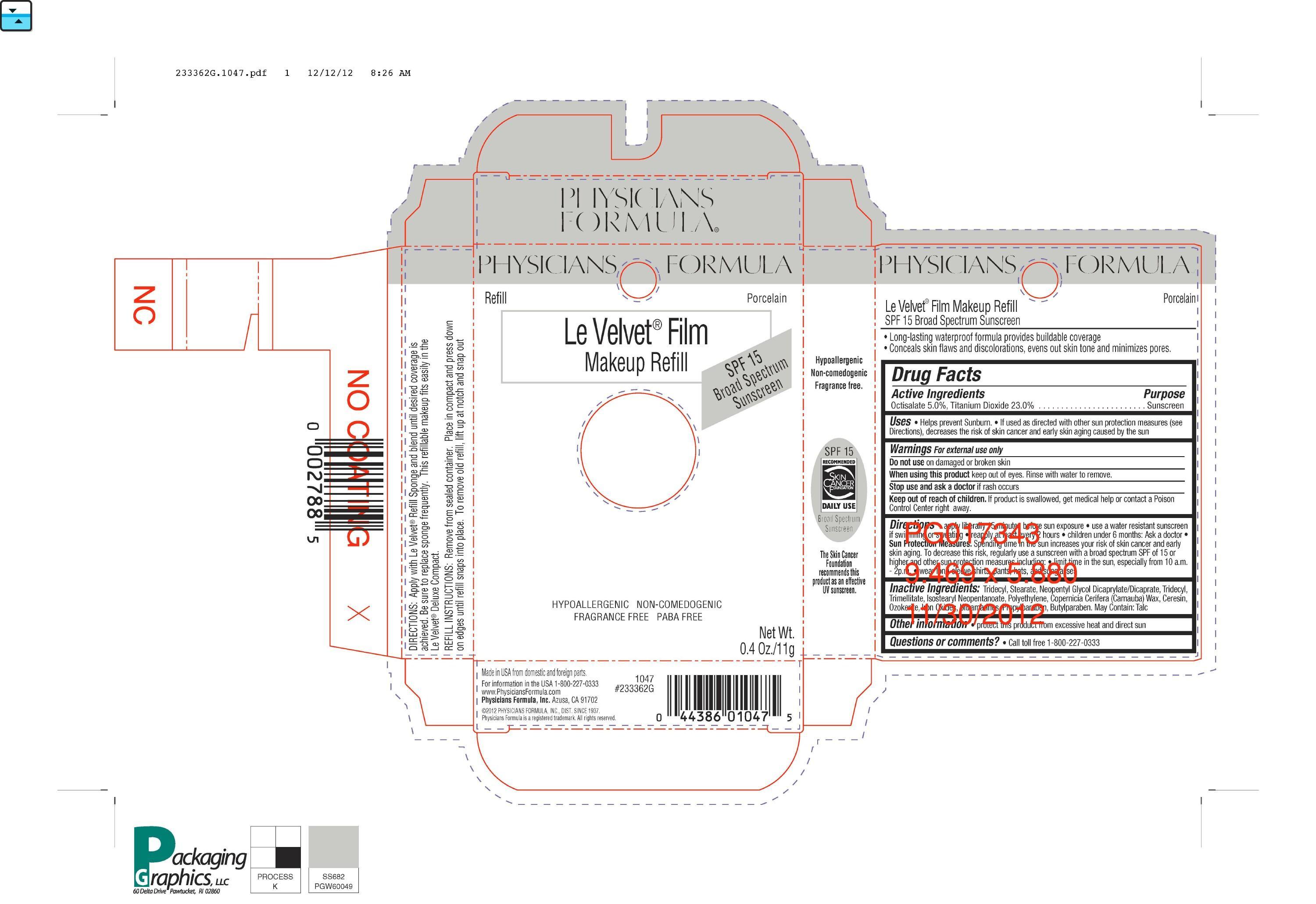 DRUG LABEL: Le Velvet Film Makeup Refill
NDC: 31645-129 | Form: PASTE
Manufacturer: Physicians Formula Inc
Category: otc | Type: HUMAN OTC DRUG LABEL
Date: 20121227

ACTIVE INGREDIENTS: OCTISALATE 5 g/100 g; TITANIUM DIOXIDE 23 g/100 g
INACTIVE INGREDIENTS: TRIDECYL STEARATE; NEOPENTYL GLYCOL DICAPRYLATE/DICAPRATE; ISOSTEARYL NEOPENTANOATE; TRIDECYL TRIMELLITATE; CARNAUBA WAX; CERESIN; FERRIC OXIDE RED; FERRIC OXIDE YELLOW; FERROSOFERRIC OXIDE; ULTRAMARINE BLUE; PROPYLPARABEN; BUTYLPARABEN; TALC

drug facts

WARNINGS AND PRECAUTIONS

Warnings: For external use only. Do not use on broken or damaged skin.

When using this product keep out of eyes. Rinse with water to remove.

Stop use and ask a doctor if rash occurs

Keep out of reach of children. If product is swallowed, get medical help or contact a Poison Control Center right away.

ACTIVE INGREDIENT

Active Ingredients: Octinoxate 7.5%, Octisalate 4.0%, Oxybenzone 4.0%

Purpose: Sunscreen